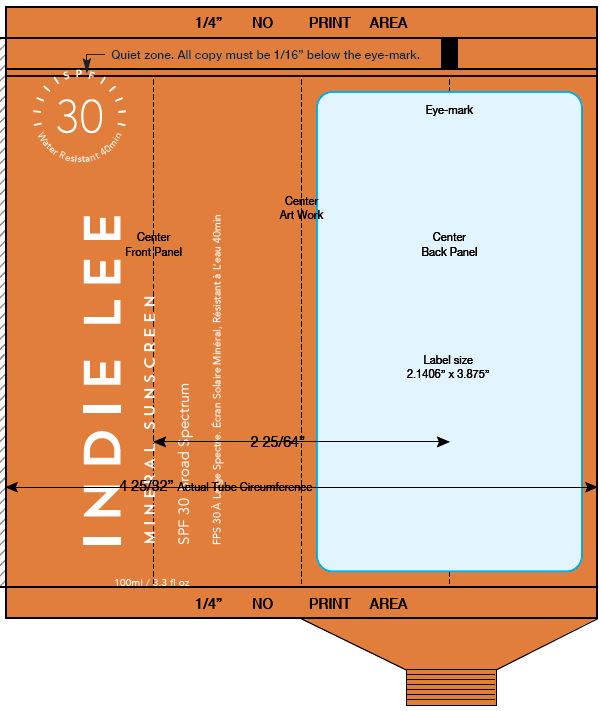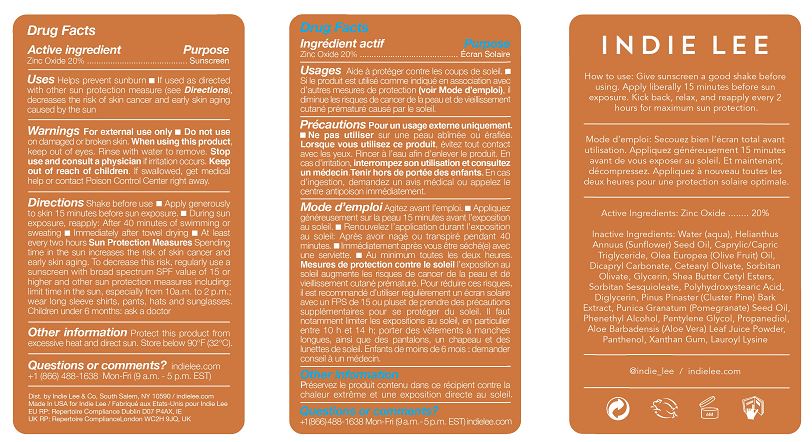 DRUG LABEL: MINERAL SUNSCREEN
NDC: 81545-101 | Form: LOTION
Manufacturer: Lee Indie & Co Inc
Category: otc | Type: HUMAN OTC DRUG LABEL
Date: 20230110

ACTIVE INGREDIENTS: ZINC OXIDE 20 g/100 mL
INACTIVE INGREDIENTS: MARITIME PINE; POMEGRANATE SEED OIL; ALOE VERA LEAF; PANTHENOL; XANTHAN GUM; PHENYLETHYL ALCOHOL; PENTYLENE GLYCOL; PROPANEDIOL; LAUROYL LYSINE; MEDIUM-CHAIN TRIGLYCERIDES; SORBITAN OLIVATE; WATER; SUNFLOWER OIL; GLYCERIN; SQUALANE; DICAPRYLYL CARBONATE; CETEARYL OLIVATE; DIGLYCERIN; SHEA BUTTER ETHYL ESTERS; SORBITAN SESQUIOLEATE; POLYHYDROXYSTEARIC ACID (2300 MW)

INDIE LEE - MINERAL SUNSCREEN SPF 30 (81545-101)

ACTIVE INGREDIENT

ZINC OXIDE 20%

PURPOSE

SUNSCREEN

USES

- HELPS PREVENT SUNBURN
- IF USED AS DIRECTED WITH OTHER SUN PROTECTION MEASURES (SEE DIRECTIONS), DECREASES THE RISK OF SKIN CANCER AND EARLY SKIN AGING CAUSED BY THE SUN.

WARNINGS

FOR EXTERNAL USE ONLY.

DO NOT USE ON DAMAGED OR BROKEN SKIN.

WHEN USING THIS PRODUCT KEEP OUT OF EYES. RINSE WITH WATER TO REMOVE.

STOP USE AND CONSULT A PHYSICIAN IF RASH OCCURS.

KEEP OUT OF REACH OF CHILDREN. IF SWALLOWED, GET MEDICAL HELP OR CONTACT A POISON CONTROL CENTER RIGHT AWAY.

DIRECTIONS

Shake before use.

- Apply generously to skin 15 minutes before sun exposure.
- During sun exposure, reapply: After 40 minutes of swimming or sweating
- Immediately after towel drying
- At least every two hours

Sun Protection Measures Spending time in the sun increases the risk of skin cancer and early skin aging. To decrease this risk, regularly use a sunscreen with broad spectrum SPF value of 15 or higher and other sun protection measures including: limit time in the sun, especially from 10a.m. to 4 p.m.; wear long sleeve shirts, pants, hats and sunglasses. Children under 6 months: ask a doctor

INACTIVE INGREDIENTS

Water (aqua), Helianthus Annuus (Sunflower) Seed Oil, Caprylic/Capric Triglyceride, Squalane, Dicapryl Carbonate, Cetearyl Olivate, Sorbitan Olivate, Glycerin, Shea Butter Cetyl Esters, Sorbitan Sesquioleate, Polyhydroxystearic Acid, Diglycerin, Pinus Pinaster (Cluster Pine) Bark Extract, Punica Granatum (Pomegranate) Seed Oil, Phenethyl Alcohol, Pentylene Glycol, Propanediol, Aloe Barbadensis (Aloe Vera) Leaf Juice Powder, Panthenol, Xanthan Gum, Lauroyl Lysine

OTHER INFORMATION

Protect this product from excessive heat and direct sun. Store below 90°F (32°C).

QUESTIONS OR COMMENTS?

INDIELEE.COM

+1 (866) 488-1638 MON-FRI (9 A.M. - 5 P.M. EST)